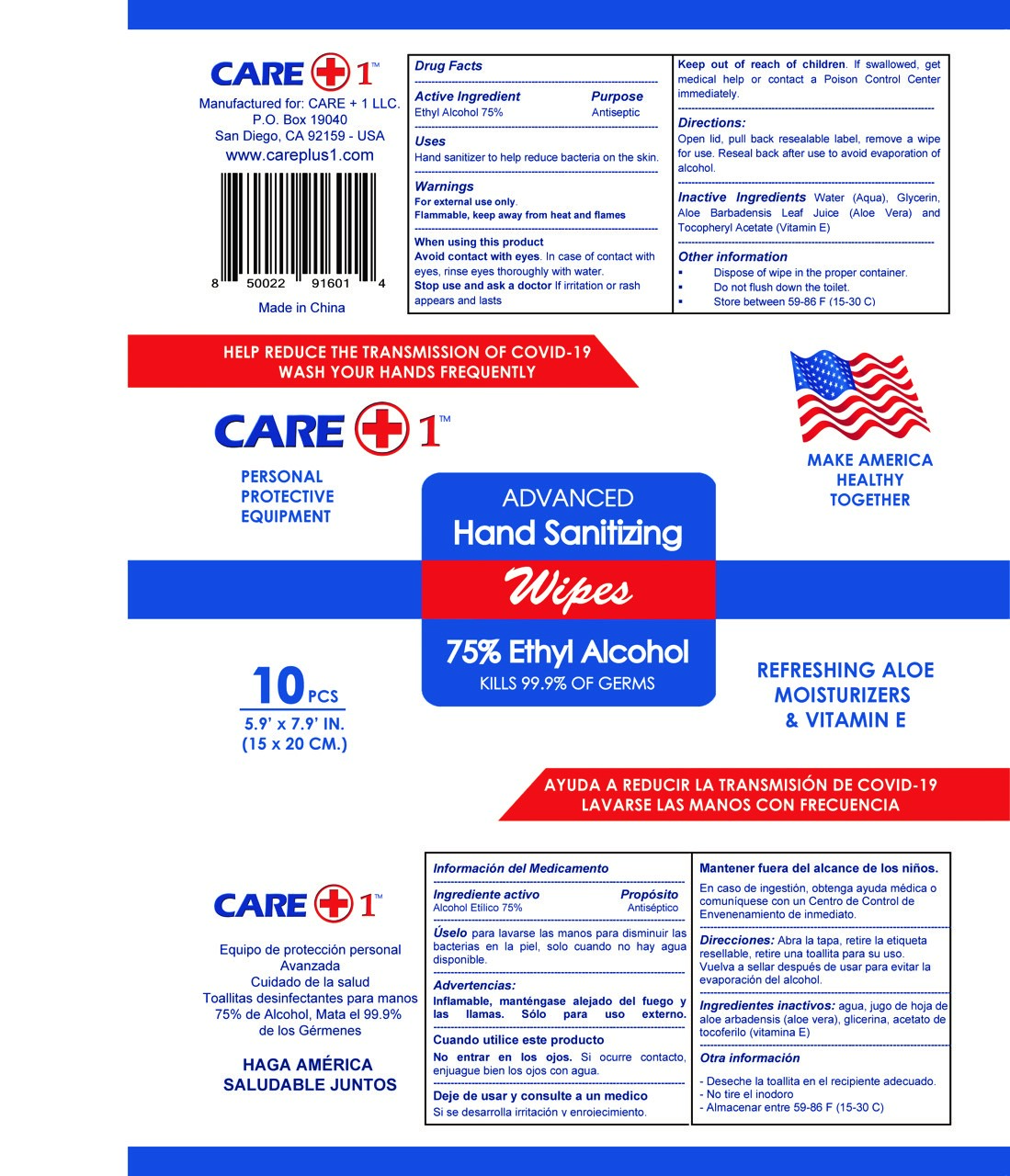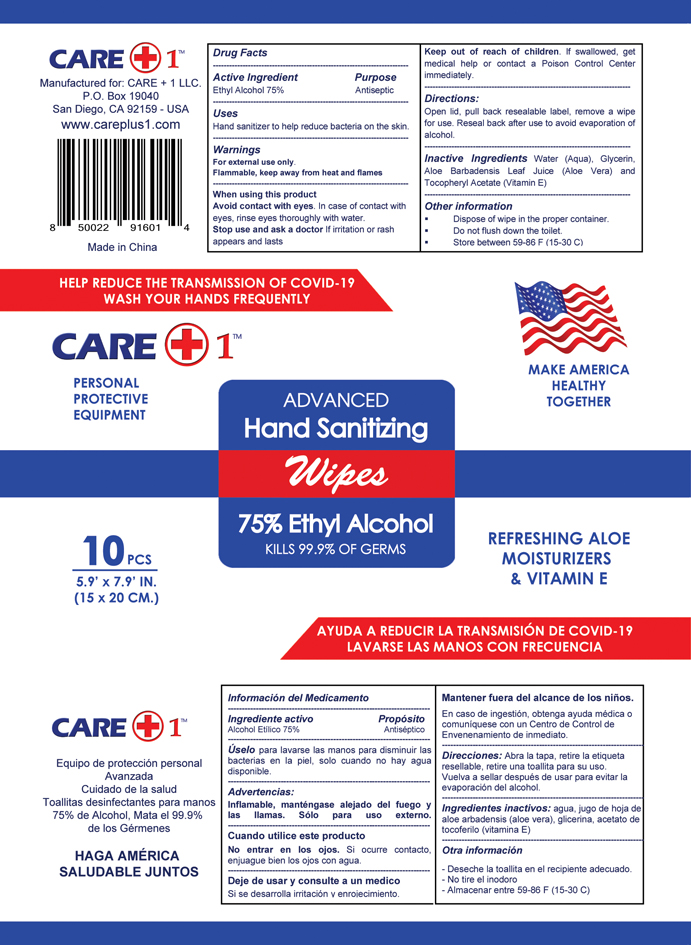 DRUG LABEL: Hand Sanitizer
NDC: 80072-002 | Form: CLOTH
Manufacturer: CARE + 1 LLC
Category: otc | Type: HUMAN OTC DRUG LABEL
Date: 20201214

ACTIVE INGREDIENTS: ALCOHOL 75 mL/100 mL
INACTIVE INGREDIENTS: .ALPHA.-TOCOPHEROL ACETATE, D- 0.0005 mL/100 mL; GLYCERIN 0.003 mL/100 mL; WATER 0.246 mL/100 mL; ALOE VERA LEAF 0.0005 mL/100 mL

HAND SANITIZER

Active Ingredient(s)

Ethyl Alcohol 75% v/v. Purpose: Antiseptic

Purpose

Antiseptic, Hand Sanitizer

Use

Hand Sanitizer to help reduce bacteria that potentially can cause disease. For use when soap and water are not available.

Warnings

For external use only. Flammable. Keep away from heat or flame

When using this product

Avoid contact with eyes. In case of contact with eyes, rinse eyes thoroughly with water.

Stop use and ask a doctor if irritation or rash appears and lasts

Keep out of reach of children. If swallowed, get medical help or contact a Poison Control Center right away.

Directions

- Open lid, pull back reseable label, remove a wipe for use.
- Reseal back after use to avoid evaporation of alcohol

Other information

- Store between 15-30C (59-86F)
- Dispose of wipes in the proper container
- Do not flush down the toilet

Inactive ingredients

water (aqua), glycerin, Aloe arbadensis leaf extract (Alove Vera), Tocopheryl acetate (Vitamin E)

This is a hand sanitizer manufactured according to the Temporary Policy for Preparation of Certain Alcohol-Based Hand Sanitizer Products During the Public Health Emergency (CoViD-19); Guidance for Industry.

The hand sanitizer is manufactured using only the following United States Pharmacopoeia (USP) grade ingredients in the preparation of the product (percentage in final product formulation) consistent with World Health Organization (WHO) recommendations:

Alcohol (75%, v/v) in an aqueous solution denatured according to Alcohol and Tobacco Tax and Trade Bureau regulations in 27 CFR part 20.
Glycerol (1.45% v/v).
Hydrogen peroxide (0.125% v/v).
Sterile distilled water or boiled cold water.
The firm does not add other active or inactive ingredients. Different or additional ingredients may impact the quality and potency of the product.

PACKAGE LABEL

NDC: 80072-002-10